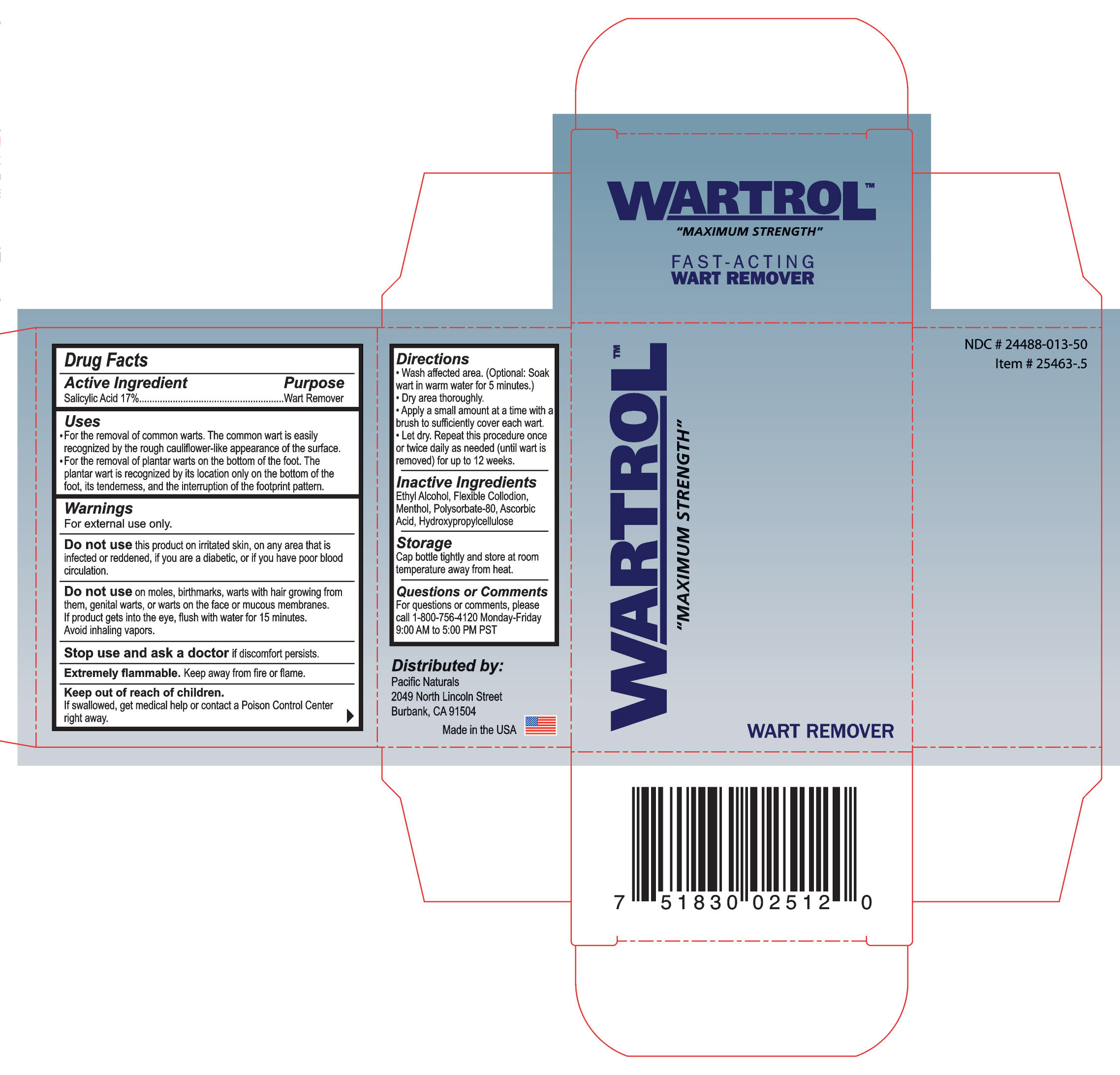 DRUG LABEL: Wartrol
NDC: 24488-013 | Form: LIQUID
Manufacturer: Pacific Naturals
Category: otc | Type: HUMAN OTC DRUG LABEL
Date: 20110901

ACTIVE INGREDIENTS: SALICYLIC ACID 2.51 mL/14.78 mL
INACTIVE INGREDIENTS: ALCOHOL; LYTTA VESICATORIA; MENTHOL; POLYSORBATE 80; ASCORBIC ACID; HYDROXYPROPYL CELLULOSE

Drug Facts

Active Ingredient

Salicylic Acid 17%

Purpose

Wart Remover

Uses

- For the removal of common warts. The common wart is easily recognized by the rough cauliflower-like appearance of the surface.
- For the removal of plantar warts on the bottom of the foot. The wart is recognized by its location only on the bottom of the foot, its tenderness, and the interruption of the footprint pattern.

Warnings

For external use only.

Do not use

this product on irritated skin, on any area that is infected or reddened, if you are diabetic, or if you have poor blood circulation.

Do not use

on moles, birthmarks, warts with hair growing from them, genital warts, or warts on teh face or mucous membranes. If product gets into the eye, flush with water for 15 minutes. Avoid inhaling vapors.

Stop use and ask a doctor

if discomfort persists.

Extremely flammable.

Keep away from fire or flame.

Keep out of reach of children.

If swallowed, get medical help pr contact a Poison Control Center right away.

Directions

- Wash affected area. (Optional: Soak wart in warm water for 5 minutes.)
- Dry area thoroughly.
- Apply a small amount at a time with a brush to sufficiently to cover each wart.
- Let dry. Repeat this procedure once or twice daily as needed (until wart is removed) for up to 12 weeks.

Inactive Ingredient

Ethyl Alcohol, Flexible Collodion, Menthol, Polysorbate-80, Ascorbic Acid, Hydroxyproylcellulose

Storage

Cap bottle tightly and store at room temperature away from heat.

Questions or Comments

For questions or comments, please call 1-800-756-4120 Monday-Friday 9:00 AM to 5:00 PM PST

PACKAGE LABEL

Placeholder Text